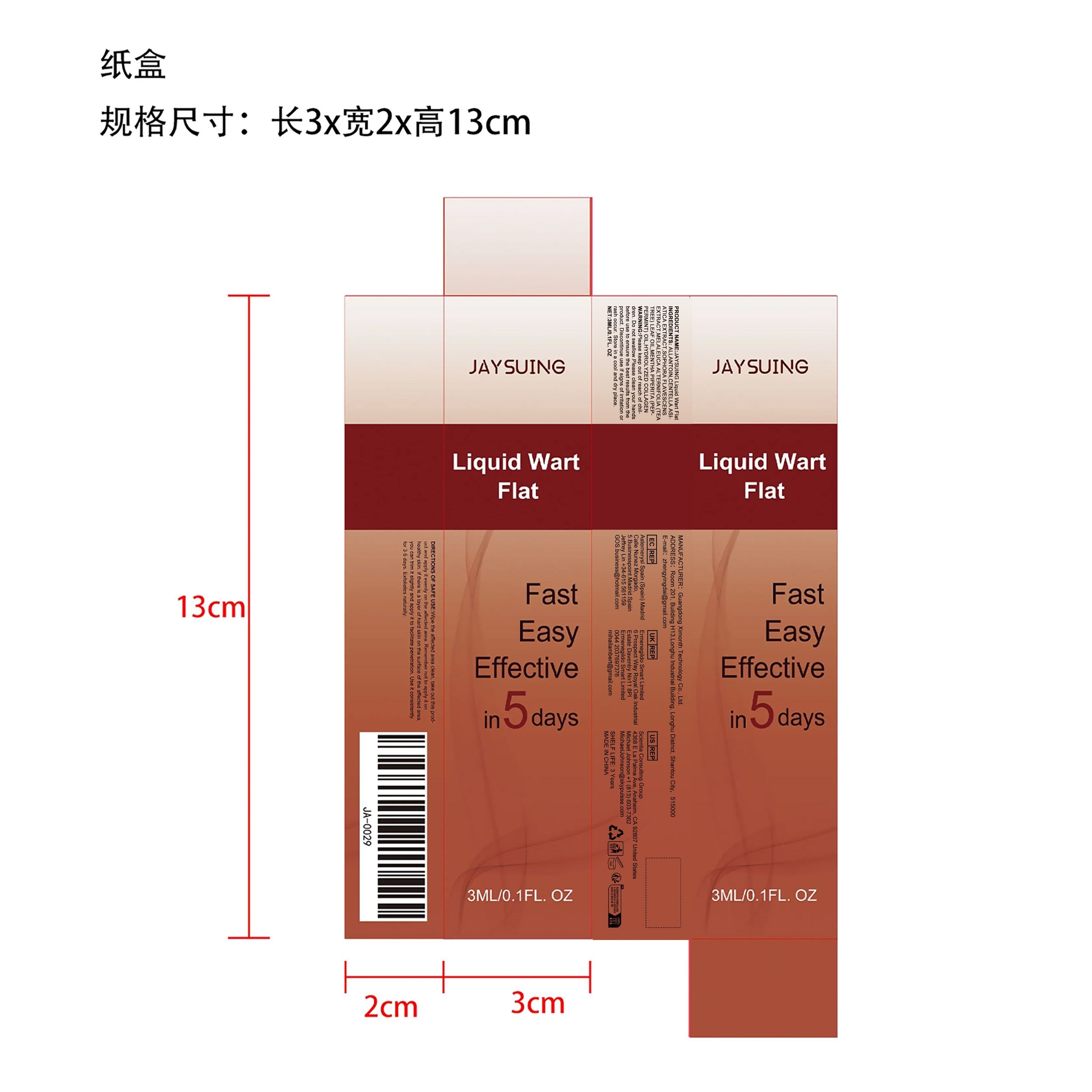 DRUG LABEL: JAYSUING Liquid Wart Flat
NDC: 84660-021 | Form: LIQUID
Manufacturer: Guangdong Ximonth Technology Co., Ltd.
Category: otc | Type: HUMAN OTC DRUG LABEL
Date: 20240924

ACTIVE INGREDIENTS: HYDROLYZED PORCINE COLLAGEN (ENZYMATIC; 3000 MW) 0.3 mg/3 mg; TEA TREE OIL 0.45 mg/3 mg; SOPHORA FLAVESCENS WHOLE 0.45 mg/3 mg; CENTELLA ASIATICA TRITERPENOIDS 0.6 mg/3 mg
INACTIVE INGREDIENTS: PEPPERMINT OIL 0.3 mg/3 mg; ALLANTOIN 0.9 mg/3 mg

Active Ingredient(s)

CENTELLA ASIATICA EXTRACT、SOPHORA FLAVESCENS EXTRACT、MELALEUCA ALTERNIFOLIA (TEATREE) LEAF OIL、MENTHA PIPERITA (PEPPERMINT) OIL、HYDROLYZED COLLAGEN

Purpose

Painless experience: Mild formula, easily remove warts and moles without causing discomfort

Use

Wipe the affected area clean, take out this product and apply it evenly on the affected area. Remember not to apply it on healthy skin. If there is a layer of hard skin on the surface of the affected area, you can trim it slightly and apply it to facilitate penetration. Use it consistently for 3-5 days. Exfoliates naturally.

Warnings

Please keep out of reach of children.Do not swallow.Please clean your hands before use to ensure the best results from the product.Discontinue use if signs of irritation or rash occur.Store in a cool and dry place.

Do not use

Discontinue use if signs of irritation or rash occur.

STOP USE

Discontinue use if signs of irritation or rash occur.

KEEP OUT OF REACH OF CHILDREN

Please keep out of reach of children. Do not swallow

STORAGE AND HANDLING

Avoid freezing and excessive heat above 40C (104F) ）
Store in a cool and dry place.

INACTIVE INGREDIENT

ALLANTOIN